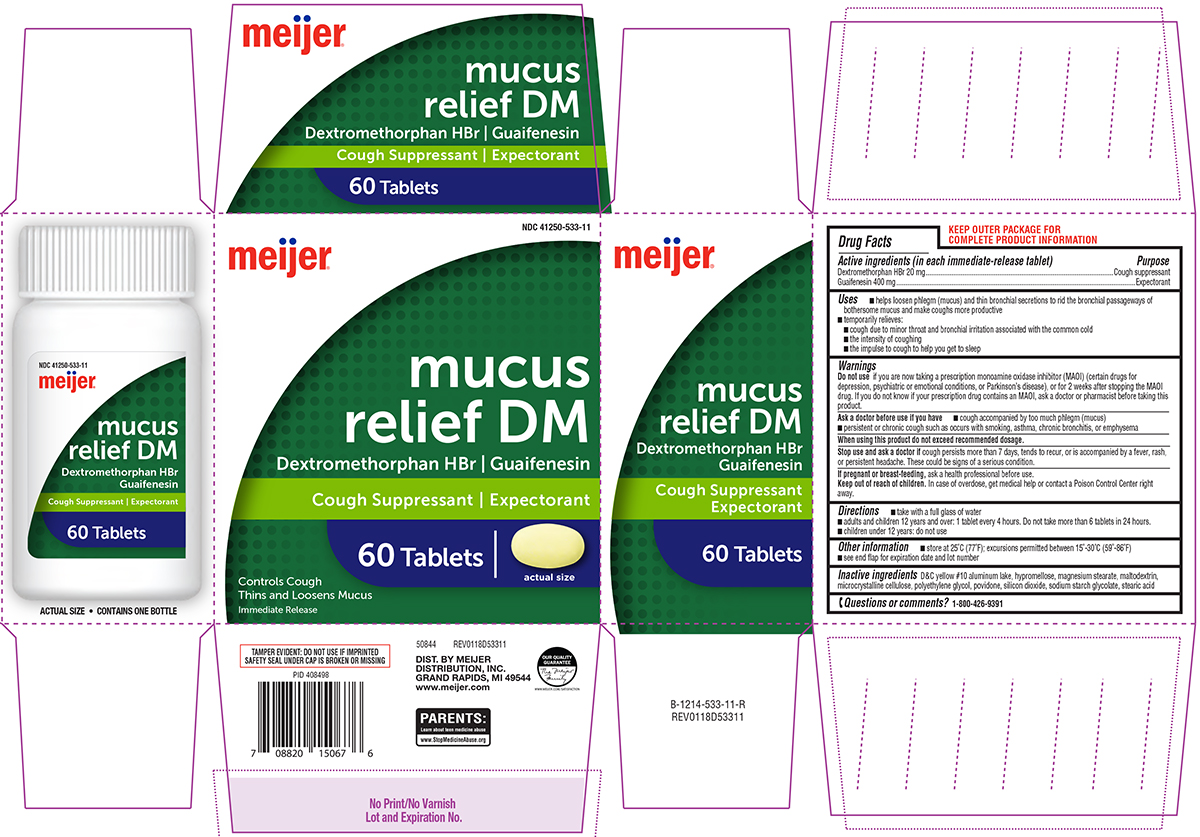 DRUG LABEL: Mucus Relief DM
NDC: 41250-533 | Form: TABLET, FILM COATED
Manufacturer: Meijer Distribution Inc
Category: otc | Type: HUMAN OTC DRUG LABEL
Date: 20251209

ACTIVE INGREDIENTS: DEXTROMETHORPHAN HYDROBROMIDE 20 mg/1 1; GUAIFENESIN 400 mg/1 1
INACTIVE INGREDIENTS: D&C YELLOW NO. 10 ALUMINUM LAKE; HYPROMELLOSE, UNSPECIFIED; MAGNESIUM STEARATE; MALTODEXTRIN; MICROCRYSTALLINE CELLULOSE; POLYETHYLENE GLYCOL, UNSPECIFIED; POVIDONE, UNSPECIFIED; SILICON DIOXIDE; SODIUM STARCH GLYCOLATE TYPE A POTATO; STEARIC ACID

Meijer 44-533 Delisted

Active ingredients (in each immediate-release tablet)

Dextromethorphan HBr 20 mg
Guaifenesin 400 mg

Purpose

Cough suppressant
Expectorant

Uses

- helps loosen phlegm (mucus) and thin bronchial secretions to rid the bronchial passageways of bothersome mucus and make coughs more productive
- temporarily relieves:
  - cough due to minor throat and bronchial irritation associated with the common cold
  - the intensity of coughing
  - the impulse to cough to help you get to sleep

Warnings

Do not use

if you are now taking a prescription monoamine oxidase inhibitor (MAOI) (certain drugs for depression, psychiatric or emotional conditions, or Parkinson’s disease), or for 2 weeks after stopping the MAOI drug. If you do not know if your prescription drug contains an MAOI, ask a doctor or pharmacist before taking this product.

Ask a doctor before use if you have

- cough accompanied by too much phlegm (mucus)
- persistent or chronic cough such as occurs with smoking, asthma, chronic bronchitis, or emphysema

When using this product

do not exceed recommended dosage.

Stop use and ask a doctor if

cough persists more than 7 days, tends to recur, or is accompanied by a fever, rash, or persistent headache. These could be signs of a serious condition.

If pregnant or breast-feeding,

ask a health professional before use.

Keep out of reach of children.

In case of overdose, get medical help or contact a Poison Control Center right away.

Directions

- take with a full glass of water
- adults and children 12 years and over: 1 tablet every 4 hours. Do not take more than 6 tablets in 24 hours.
- children under 12 years: do not use

Other information

- store at 25°C (77°F); excursions permitted between 15°-30°C (59°-86°F)
- see end flap for expiration date and lot number

Inactive ingredients

D&C yellow #10 aluminum lake, hypromellose, magnesium stearate, maltodextrin, microcrystalline cellulose, polyethylene glycol, povidone, silicon dioxide, sodium starch glycolate, stearic acid

Questions or comments?

1-800-426-9391

Principal Display Panel

NDC 41250-533-11

meijer®

mucus
relief DM
Dextromethorphan HBr | Guaifenesin
Cough Suppressant | Expectorant

Controls Cough
Thins and Loosens Mucus
Immediate Release

60 Tablets

actual size

TAMPER EVIDENT: DO NOT USE IF IMPRINTED
SAFETY SEAL UNDER CAP IS BROKEN OR MISSING

50844 REV0118D53311

DIST. BY MEIJER
DISTRIBUTION, INC.
GRAND RAPIDS, MI 49544
www.meijer.com

Our quality
Guarantee

PARENTS:
Learn about teen medicine abuse
www.StopMedicineAbuse.org

Meijer 44-533